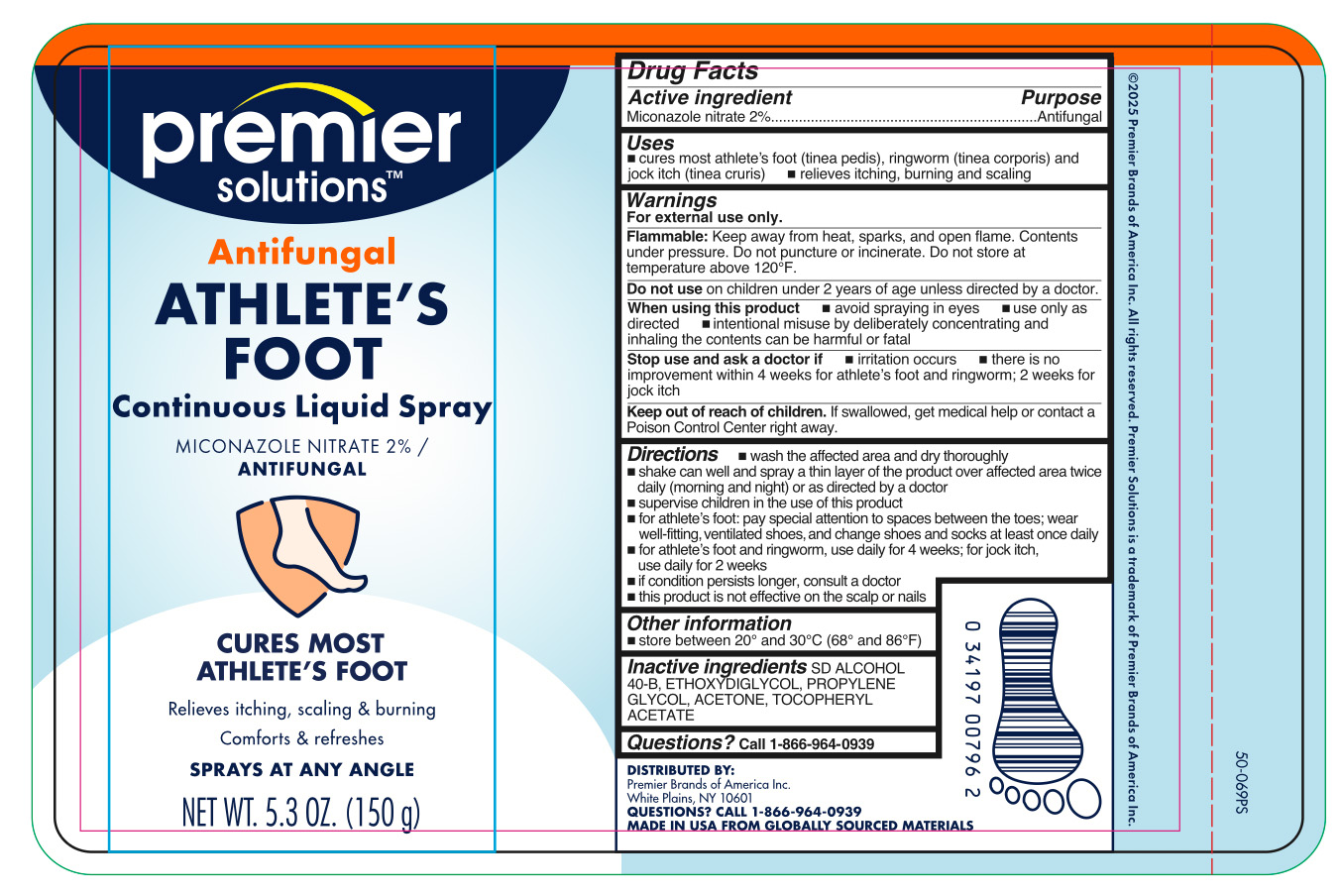 DRUG LABEL: Miconazole nitrate
NDC: 56104-903 | Form: AEROSOL, SPRAY
Manufacturer: Premier Brands of America Inc.
Category: otc | Type: HUMAN OTC DRUG LABEL
Date: 20251103

ACTIVE INGREDIENTS: MICONAZOLE NITRATE 20 mg/1 g
INACTIVE INGREDIENTS: ACETONE; ETHOXYDIGLYCOL; PROPYLENE GLYCOL; ALCOHOL; ALPHA-TOCOPHEROL ACETATE

Premier Solutions Antifungal Miconazole Liquid Continuous Spray

Active ingredient

Miconazole nitrate 2%

Purpose

Antifungal

Uses

- cures most athlete's foot (linea pedis), ringworm (linea corporis) and jock itch (linea cruris)
- relieves itching, burning and scaling

Warnings

For external use only.

Flammable:

Keep away from heat, sparks, and open flame. Contents under pressure.Do not puncture or incinerate. Do not store at temperature above 120ºF.

When using this product

- avoid spraying in eyes
- use only as directed
- intentional misuse by deliberately concentrating and inhaling the contents can be harmful or fatal.

Stop use and ask a doctor if

- irritation occurs
- there is no improvement within 4 weeks for athlete's foot and ringworm; 2 weeks for jock itch

Keep out of reach of children.

If swallowed, get medical help or contact a Poison Control Center right away.

Directions

- wash the affected area and dry thoroughly
- shake can well and spray a thin layer of the product over affected area twice daily (morning and night) or as directed by a doctor
- supervise children in the use of this product
- for athlete's foot: pay special attention to spaces between the toes; wear well-fitting, ventilated shoes, and change shoes and socks at least once daily
- for athlete's foot and ringworm, use daily for 4 weeks; for jock itch, use daily for 2 weeks
- if conditions persist, consult a doctor
- this product is not effective on the scalp or nails

Other information

store between 20º and 30ºC (68º and 86ºF)

Inactive ingredients

SD ALCOHOL 40-B, ETHOXYGLYCOL, PROPYLENE GLYCOL, ACETONE, TOCOPHERYL ACETATE

Questions?

call 1-866-964-0939

RECENT MAJOR CHANGES

.

Principal Display Panel

premier

solutions

Antifungal

ATHLETE'S

FOOT

Continuous Liquid Spray

MICONAZOLE NITRATE 2% /

ANTIFUNGAL

CURES MOST
ATHLETE'S FOOT

Relieves itching, scaling & burning

Comforts & refreshes

SPRAYS AT ANY ANGLE

NET WT. 5.3 OZ. (150g)